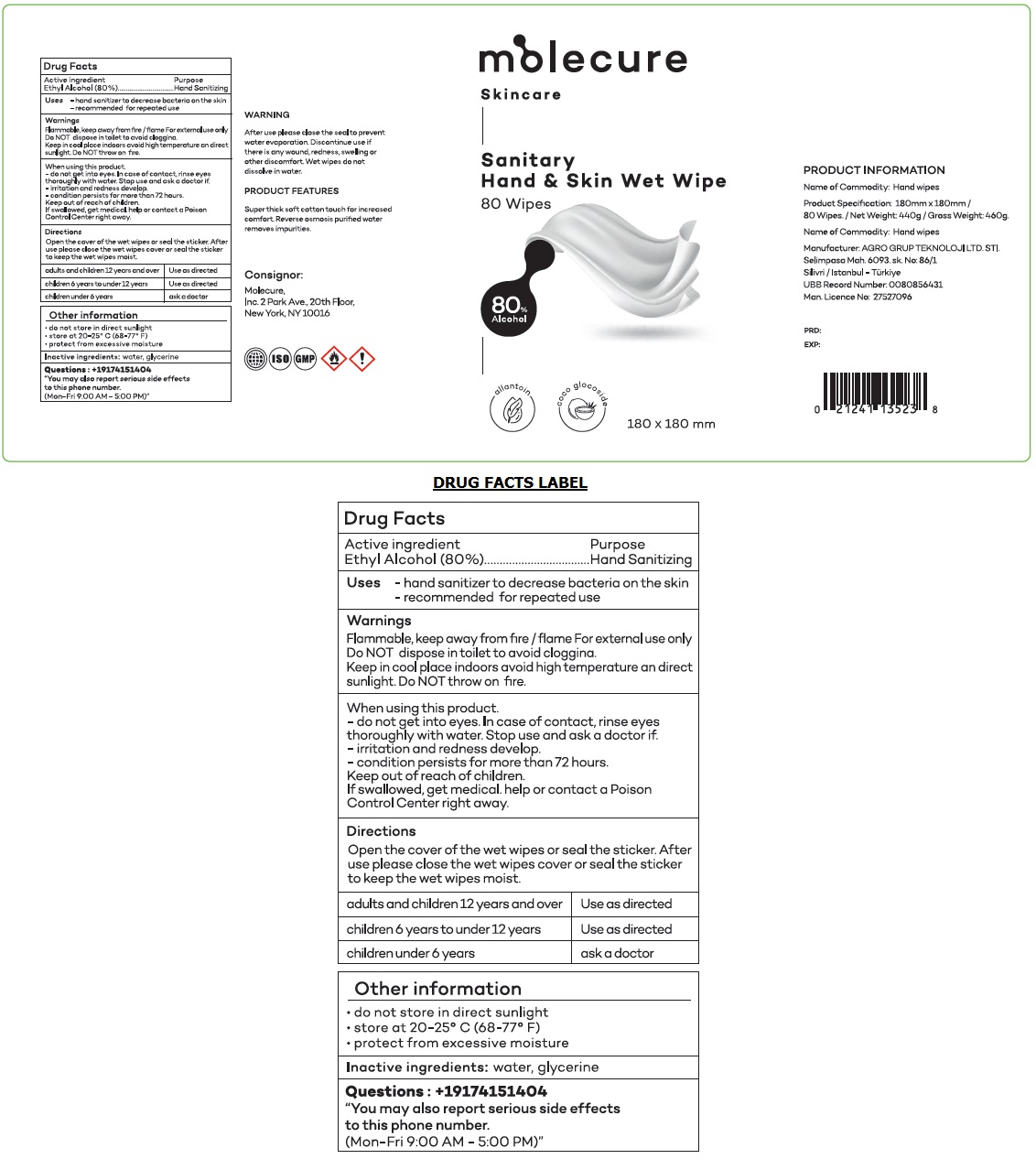 DRUG LABEL: Molecure Skincare
NDC: 79781-216 | Form: CLOTH
Manufacturer: Molecule Koruyucu Saglik Urunleri Sanayi Ve Ticaret Anonim Sirketi
Category: otc | Type: HUMAN OTC DRUG LABEL
Date: 20201106

ACTIVE INGREDIENTS: ALCOHOL 80 mL/100 mL
INACTIVE INGREDIENTS: WATER; GLYCERIN

molecure Skincare Sanitary Hand & Skin Wet Wipe

Active ingredient

Ethyl Alcohol (80%)

Purpose

Hand Sanitizing

Uses

- hand sanitizer to decrease bacteria on the skin

- recommended for repeated use

Warnings

Flammable, keep away from fire / flame For external use only

Do NOT dispose in toilet to avoid clogging.

Keep in cool place indoors avoid high temperature and direct sunlight. Do NOT throw on fire.

When using this product.

- do not get into eyes. In case of contact, rinse eyes thoroughly with water. Stop use and ask a doctor if.
- irritation and redness develop.
- condition persists for more than 72 hours.

Keep out of reach of children.

If swallowed, get medical help or contact a Poison Control Center right away.

Directions

Open the cover of the wet wipes or seal the sticker. After use please close the wet wipes cover or seal the sticker to keep the wet wipes moist.

adults and children 12 years and over | Use as directed
children 6 years to under 12 years | Use as directed
children under 6 years | ask a doctor

Other information

• do not store in direct sunlight

• store at 20-25° C (68-77° F)

• protect from excessive moisture

Inactive ingredients:

water, glycerine

Questions: +19174151404

"You may also report serious side effects to this phone number.

(Mon-Fri 9:00 AM - 5:00 PM)"

Sanitary Hand & Skin Wet Wipe

allantoin

coco glocoside

WARNING

After use please close the seal to prevent water evaporation. Discontinue use if there is any wound, redness, swelling or other discomfort. Wet wipes do not dissolve in water.

PRODUCT FEATURES

Super thick soft cotton touch for increased comfort. Reverse osmosis purified water removes impurities.

Consignor:

Molecure,

Inc. 2 Park Ave., 20th Floor,

New York, NY 10016

ISO GMP

PRODUCT INFORMATION

Name of Commodity: Hand wipes

Product Specification: 180mm x 180mm / 80 wipes. / Net Weight: 440g / Gross Weight: 460g.

Manufacturer: AGRO GRUP TEKNOLOJI LTD. STI.

Selimpasa Mah. 6093.sk. No: 86/1

Silivri / Istanbul - Türkiye

UBB Record Number: 0080856431

Man. License No: 27527096